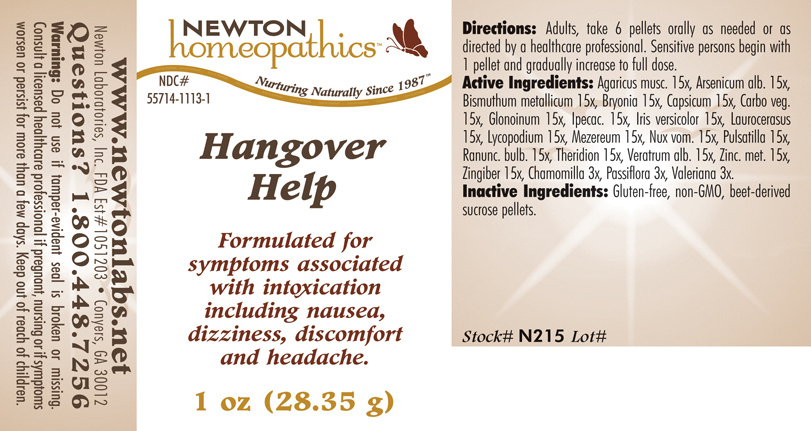 DRUG LABEL: Hangover Help 
NDC: 55714-1113 | Form: PELLET
Manufacturer: Newton Laboratories, Inc.
Category: homeopathic | Type: HUMAN OTC DRUG LABEL
Date: 20110301

ACTIVE INGREDIENTS: Amanita Muscaria Var. Muscaria Fruiting Body 15 [hp_X]/1 g; Arsenic Trioxide 15 [hp_X]/1 g; Bismuth 15 [hp_X]/1 g; Bryonia Alba Root 15 [hp_X]/1 g; Capsicum 15 [hp_X]/1 g; Activated Charcoal 15 [hp_X]/1 g; Nitroglycerin 15 [hp_X]/1 g; Ipecac 15 [hp_X]/1 g; Iris Versicolor Root 15 [hp_X]/1 g; Prunus Laurocerasus Leaf 15 [hp_X]/1 g; Lycopodium Clavatum Spore 15 [hp_X]/1 g; Daphne Mezereum Bark 15 [hp_X]/1 g; Strychnos Nux-vomica Seed 15 [hp_X]/1 g; Pulsatilla Vulgaris 15 [hp_X]/1 g; Ranunculus Bulbosus 15 [hp_X]/1 g; Theridion Curassavicum 15 [hp_X]/1 g; Veratrum Album Root 15 [hp_X]/1 g; Zinc 15 [hp_X]/1 g; Ginger 15 [hp_X]/1 g; Matricaria Recutita 3 [hp_X]/1 g; Passiflora Incarnata Flowering Top 3 [hp_X]/1 g; Valerian 3 [hp_X]/1 g
INACTIVE INGREDIENTS: Sucrose

Hangover Help

INDICATIONS & USAGE SECTION

Hangover Help Formulated for symptoms associated with intoxication including nausea, dizziness, discomfort and headache.

DOSAGE & ADMINISTRATION SECTION

Directions: Adults, take 6 pellets orally as needed or as directed by a healthcare professional. Sensitive persons begin with 1 pellet and gradually increase to full dose.

OTC - ACTIVE INGREDIENT SECTION

Agaricus musc. 15x, Arsenicum alb. 15x, Bismuthum metallicum 15x, Bryonia 15x, Capsicum 15x, Carbo veg.15x, Glonoinum 15x, Ipecac. 15x, Iris versicolor 15x, Laurocerasus 15x, Lycopodium 15x, Mezereum 15x, Nux vom. 15x, Pulsatilla 15x, Ranunc. bulb. 15x, Theridion 15x, Veratrum alb. 15x, Zinc. met. 15x, Zingiber 15x, Chamomilla 3x, Passiflora 3x, Valeriana 3x.

OTC - PURPOSE SECTION

Formulated for symptoms associated with intoxication including nausea, dizziness, discomfort and headache.

INACTIVE INGREDIENT SECTION

Inactive Ingredients: Gluten-free, non-GMO, beet-derived sucrose pellets.

QUESTIONS SECTION

www.newtonlabs.net Newton Laboratories, Inc. FDA Est # 1051203 - Conyers, GA 30012
Questions? 1.800.448.7256

WARNINGS SECTION

Warning: Do not use if tamper - evident seal is broken or missing. Consult a licensed healthcare professional if pregnant, nursing or if symptoms worsen or persist for more than a few days. Keep out of reach of children.

OTC - PREGNANCY OR BREAST FEEDING SECTION

Consult a licensed healthcare professional if pregnant, nursing or if symptoms worsen or persist for more than a few days.

OTC - KEEP OUT OF REACH OF CHILDREN SECTION

Keep out of reach of children.